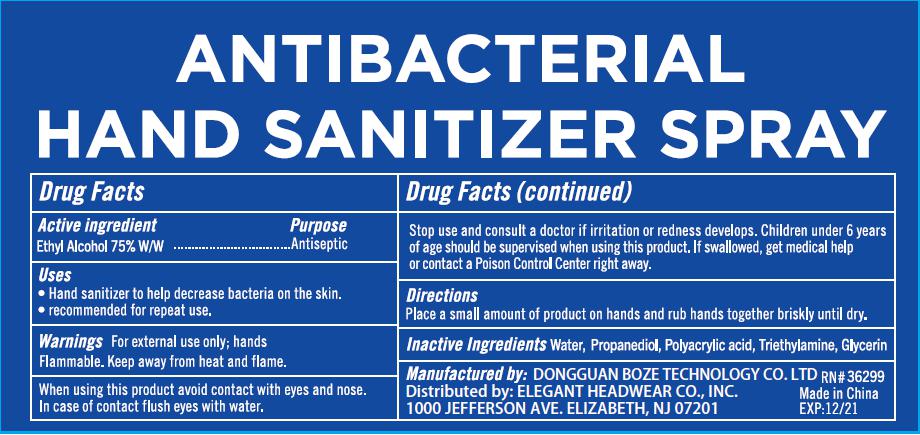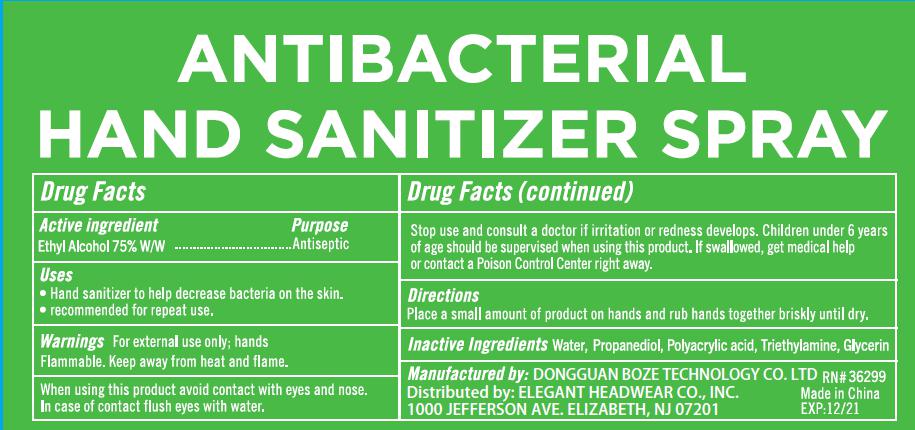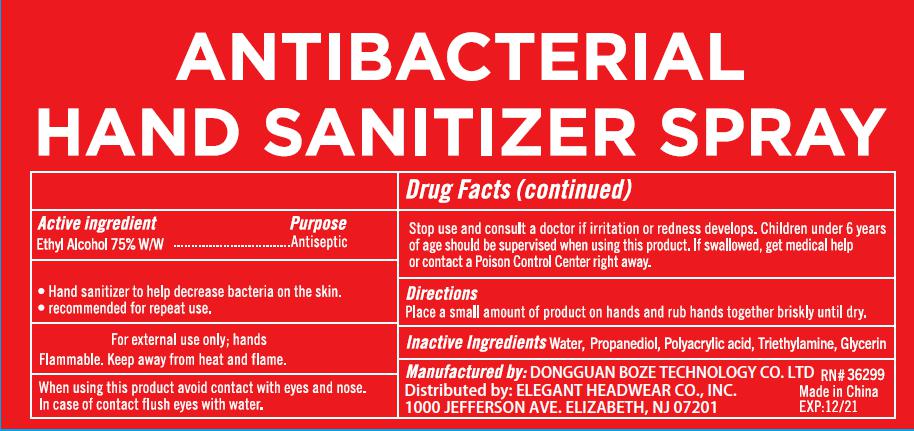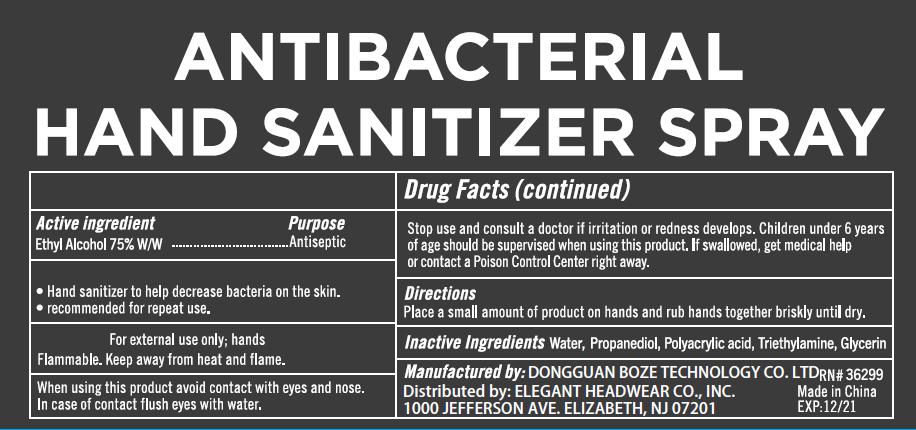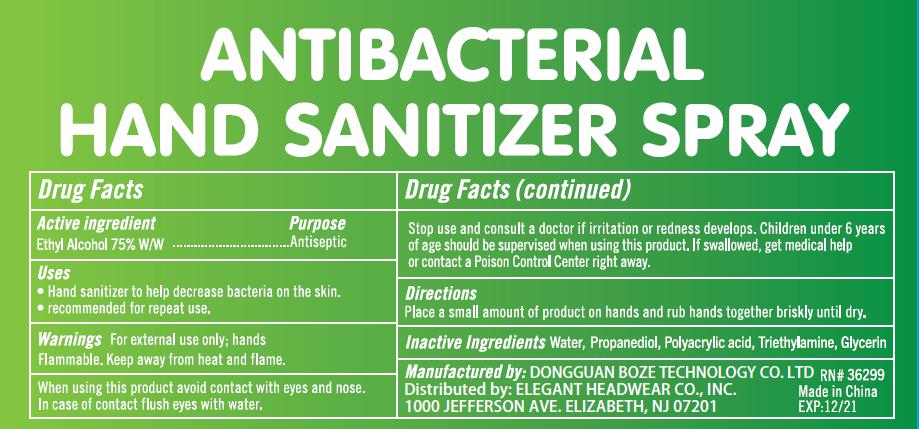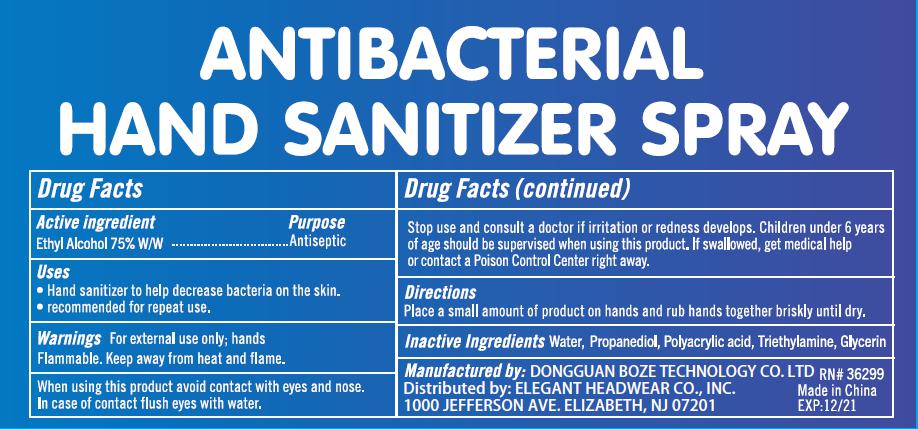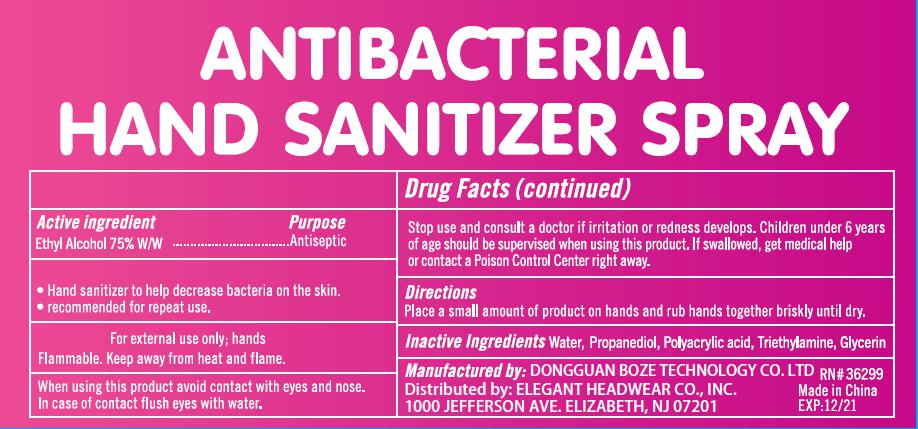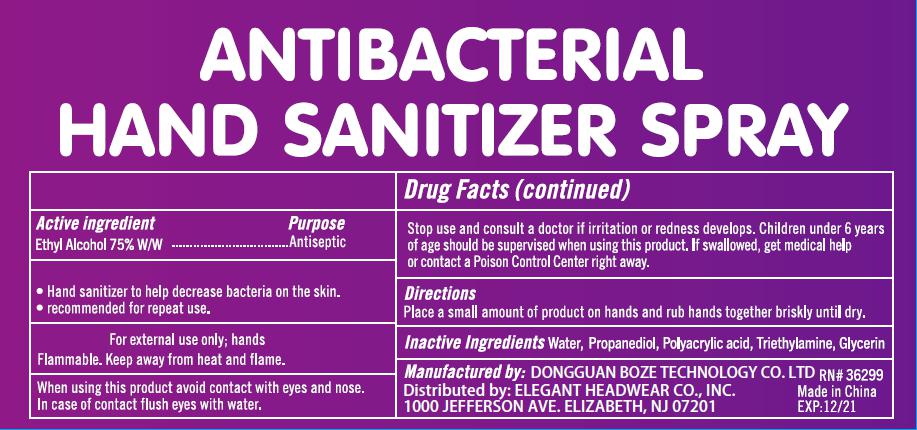 DRUG LABEL: ANTIBACTERIAL HAND SANITIZER
NDC: 78634-002 | Form: LIQUID
Manufacturer: Dongguan Boze Technology Co., LTD
Category: otc | Type: HUMAN OTC DRUG LABEL
Date: 20200717

ACTIVE INGREDIENTS: ALCOHOL 75.15 mL/100 mL
INACTIVE INGREDIENTS: GLYCERIN 0.4 mL/100 mL; PROPYLENE GLYCOL 0.16 mL/100 mL; WATER 23.905 mL/100 mL; CUPRIC TRIETHANOLAMINE 0.3 mL/100 mL; POLYACRYLIC ACID (250000 MW) 0.085 mL/100 mL

ANTIBACTERIAL HAND SANITIZER SPRAY

Active ingredient

Ethyl Alcohol 75% W/W

Purpose

Antiseptic

Use

Hand Sanitizer to help decrease bacteria on the skin.

Recommended for repeat use.

Warnings

For external use only. Flammable. Keep away from heat or flame

When using this product avoid contact with eyes and nose. In case of contact flush eyes with water.

Keep out of reach of children

Stop use and consult a doctor if irritation or redness develops. Children under 6 years of age should be supervised when using this product. If swallowed, get medical help or contact a Poison Control Center right away.

Directions

Place a small amount of product on hands and rub hands together briskly until dry.

Inactive ingredients

Water,propylene glycol,polyacrylic acid,glycerin,triethanolamine

Other information

Manufactured by: Dongguan Boze Technology Co., LTD

Distributed by: ABG ACCESSORIES INC / ELEGANT HEADWEAR CO., INC.

1000 JEFFERSON AVE, ELIZABETH, NJ 07201

Package Label

10 ML IN 1 BOTTLE NDC: 78634-002-01